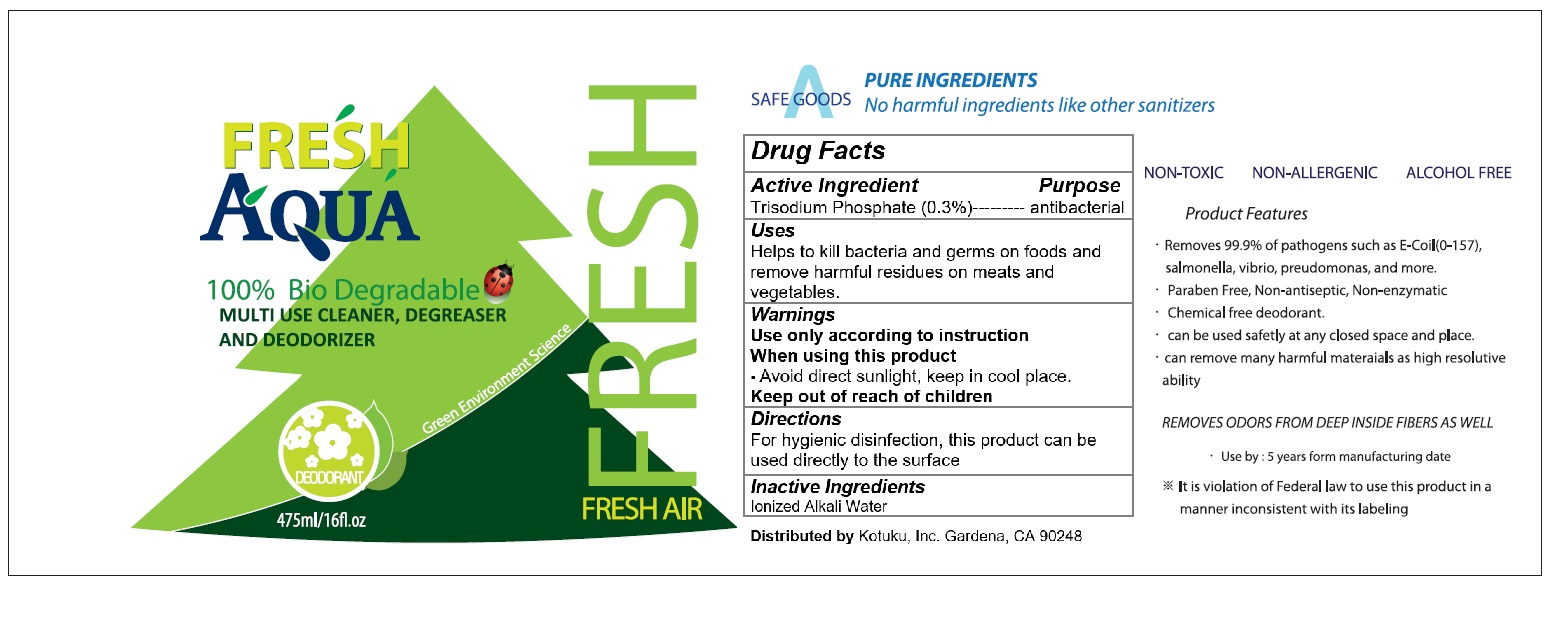 DRUG LABEL: FRESH AQUA
NDC: 70610-105 | Form: LIQUID
Manufacturer: KOTUKU INC.
Category: otc | Type: HUMAN OTC DRUG LABEL
Date: 20180814

ACTIVE INGREDIENTS: SODIUM PHOSPHATE, TRIBASIC, DODECAHYDRATE 1.425 g/475 mL
INACTIVE INGREDIENTS: WATER

FRESH AQUA